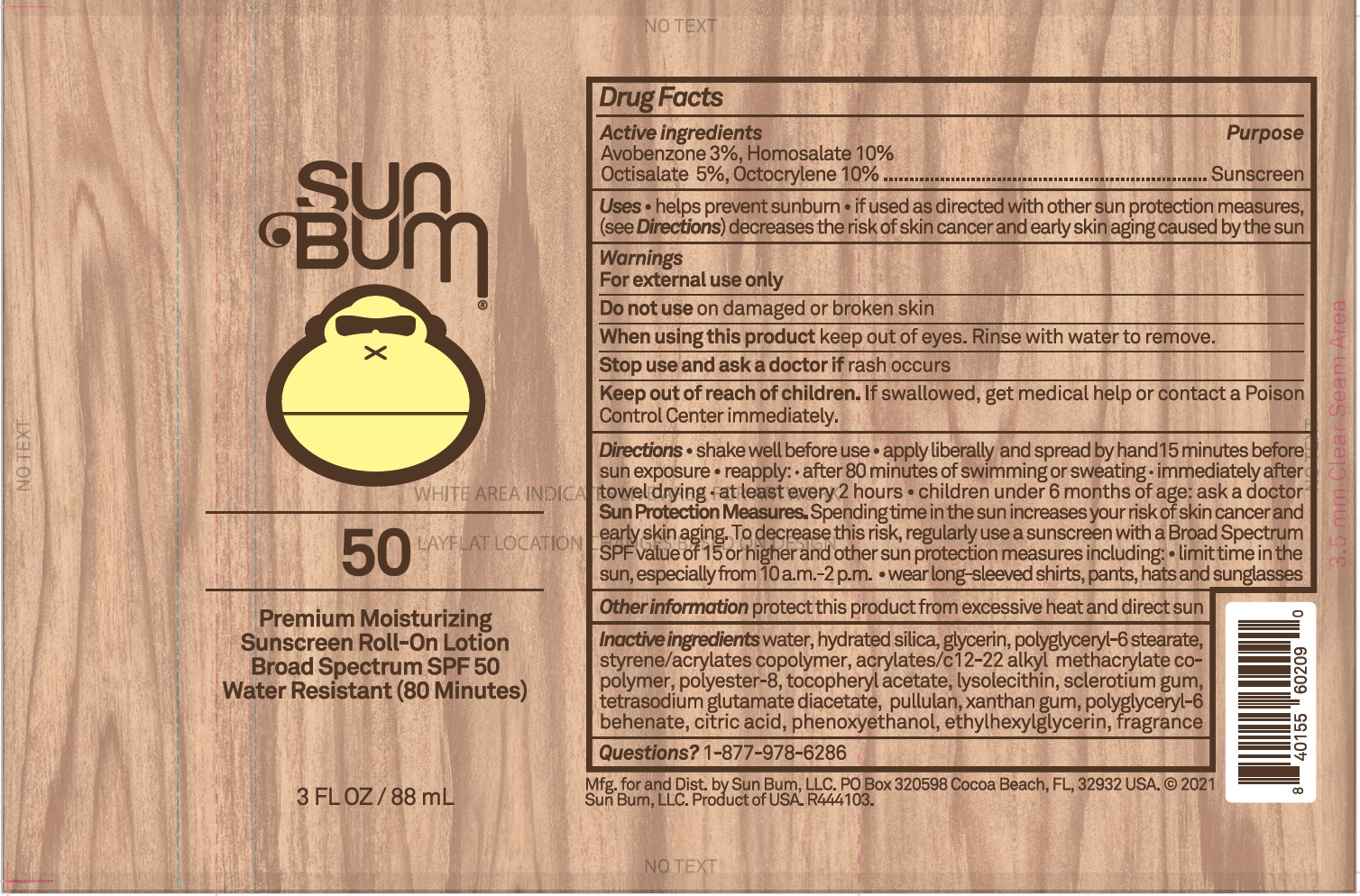 DRUG LABEL: Sun Bum Premium Moisturizing Sunscreen Roll On SPF 50
NDC: 69039-642 | Form: LOTION
Manufacturer: Sun Bum LLC
Category: otc | Type: HUMAN OTC DRUG LABEL
Date: 20220204

ACTIVE INGREDIENTS: AVOBENZONE 30 mg/1 mL; HOMOSALATE 100 mg/1 mL; OCTISALATE 50 mg/1 mL; OCTOCRYLENE 100 mg/1 mL
INACTIVE INGREDIENTS: WATER; HYDRATED SILICA; GLYCERIN; POLYGLYCERYL-6 STEARATE; .ALPHA.-TOCOPHEROL ACETATE; LYSOPHOSPHATIDYLCHOLINE, SOYBEAN; BETASIZOFIRAN; TETRASODIUM GLUTAMATE DIACETATE; PULLULAN; XANTHAN GUM; POLYGLYCERYL-6 BEHENATE; CITRIC ACID MONOHYDRATE; PHENOXYETHANOL; ETHYLHEXYLGLYCERIN; POLYESTER-8 (1400 MW, CYANODIPHENYLPROPENOYL CAPPED)

Sun Bum Premium Moisturizing Sunscreen Roll On Lotion SPF 50

Active ingredients

Avobenzone 3%, Homosalte 10%
Octisalate 5%, Octocrylene 10%

Purpose

Sunscreen

Uses

- helps prevent sunburn
- if used as directed with other sun protection measures, (see Directions) decreases the risk of skin cancer and early skin aging caused by the sun

Warnings

For external use only

Do not use

on damaged or broken skin

When using this product

keep out of eyes. Rinse with water to remove.

Stop use and ask a doctor if

rash occurs

Keep out of reach of children.

If swallowed, get medical help or contact a Poison Control Center immediately.

Directions

• shake well before use • apply liberally and spread by hand15 minutes before sun exposure • reapply: • after 80 minutes of swimming or sweating • immediately after towel drying • at least every 2 hours • children under 6 months of age: ask a doctor Sun Protection Measures. Spending time in the sun increases your risk of skin cancer and early skin aging. To decrease this risk, regularly use a sunscreen with a Broad Spectrum SPF value of 15 or higher and other sun protection measures including: • limit time in the sun, especially from 10 a.m.-2 p.m. • wear long-sleeved shirts, pants, hats and sunglasses

Other information

protect this product from excessive heat and direct sun

Inactive ingredients

water, hydrated silica, glycerin, polyglyceryl-6 stearate, styrene/acrylates copolymer, acrylates/c 12-22 alkyl methacrylate copolymer, polyster-8, tocopheryl acetate, lysolecithin, sclerotium gum, tetrasodium glutamate diacetate, pullulan, xanthan gum, polyglyceryl-6 behenate, citric acid, phenoxyethanol, ethylhexylglycerin, fragrance

Questions?

1-877-978-6286